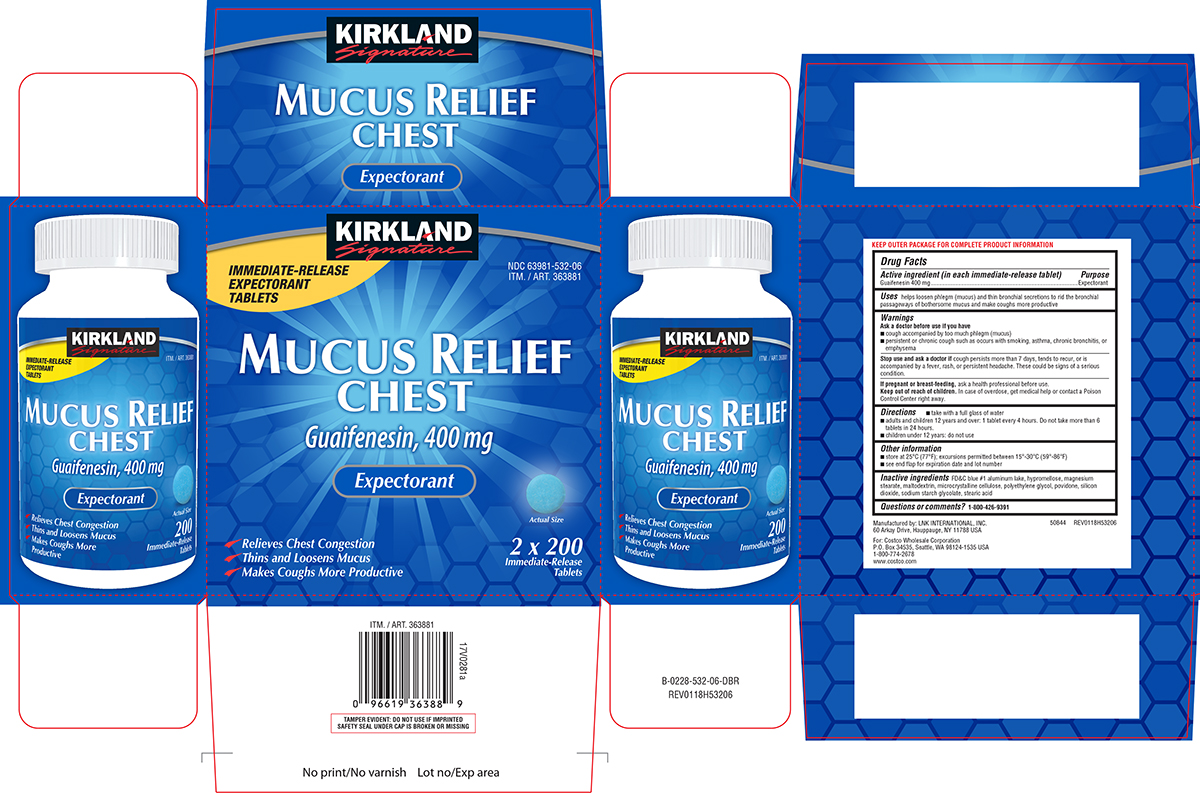 DRUG LABEL: Mucus Relief
NDC: 63981-532 | Form: TABLET, FILM COATED
Manufacturer: COSTCO WHOLESALE CORPORATION
Category: otc | Type: HUMAN OTC DRUG LABEL
Date: 20251115

ACTIVE INGREDIENTS: GUAIFENESIN 400 mg/1 1
INACTIVE INGREDIENTS: FD&C BLUE NO. 1 ALUMINUM LAKE; HYPROMELLOSE, UNSPECIFIED; MAGNESIUM STEARATE; MALTODEXTRIN; MICROCRYSTALLINE CELLULOSE; POLYETHYLENE GLYCOL, UNSPECIFIED; POVIDONE, UNSPECIFIED; SILICON DIOXIDE; SODIUM STARCH GLYCOLATE TYPE A POTATO; STEARIC ACID

Kirkland 44-532

Active ingredient (in each immediate-release tablet)

Guaifenesin 400 mg

Purpose

Expectorant

Uses

helps loosen phlegm (mucus) and thin bronchial secretions to rid the bronchial passageways of bothersome mucus and make coughs more productive

Warnings

Ask a doctor before use if you have

- cough accompanied by too much phlegm (mucus)
- persistent or chronic cough such as occurs with smoking, asthma, chronic bronchitis, or emphysema

Stop use and ask a doctor if

cough persists more than 7 days, tends to recur, or is accompanied by a fever, rash, or persistent headache. These could be signs of a serious condition.

If pregnant or breast-feeding,

ask a health professional before use.

Keep out of reach of children.

In case of overdose, get medical help or contact a Poison Control Center right away.

Directions

- take with a full glass of water
- adults and children 12 years and over: 1 tablet every 4 hours. Do not take more than 6 tablets in 24 hours.
- children under 12 years: do not use

Other information

- store at 25ºC (77ºF); excursions permitted between 15º-30ºC (59º-86ºF)
- see end flap for expiration date and lot number

Inactive ingredients

FD&C blue #1 aluminum lake, hypromellose, magnesium stearate, maltodextrin, microcrystalline cellulose, polyethylene glycol, povidone, silicon dioxide, sodium starch glycolate, stearic acid

Questions or comments?

1-800-426-9391

Principal Display Panel

KIRKLAND
Signature

IMMEDIATE-RELEASE
EXPECTORANT
TABLETS

NDC 63981-532-06
ITM. / ART. 363881

MUCUS RELIEF
CHEST
Guaifenesin, 400 mg
Expectorant

Actual Size

✔Relieves Chest Congestion

✔Thins and Loosens Mucus

✔Makes Coughs More Productive

2 x 200
Immediate-Release
Tablets

TAMPER EVIDENT: DO NOT USE IF IMPRINTED
SAFETY SEAL UNDER CAP IS BROKEN OR MISSING

50844 REV0118H53206
Manufactured by: LNK INTERNATIONAL, INC.
60 Arkay Drive, Hauppauge, NY 11788 USA

For: Costco Wholesale Corporation
P.O. Box 34535, Seattle, WA 98124-1535 USA
1-800-774-2678
www.costco.com

Kirkland 44-532